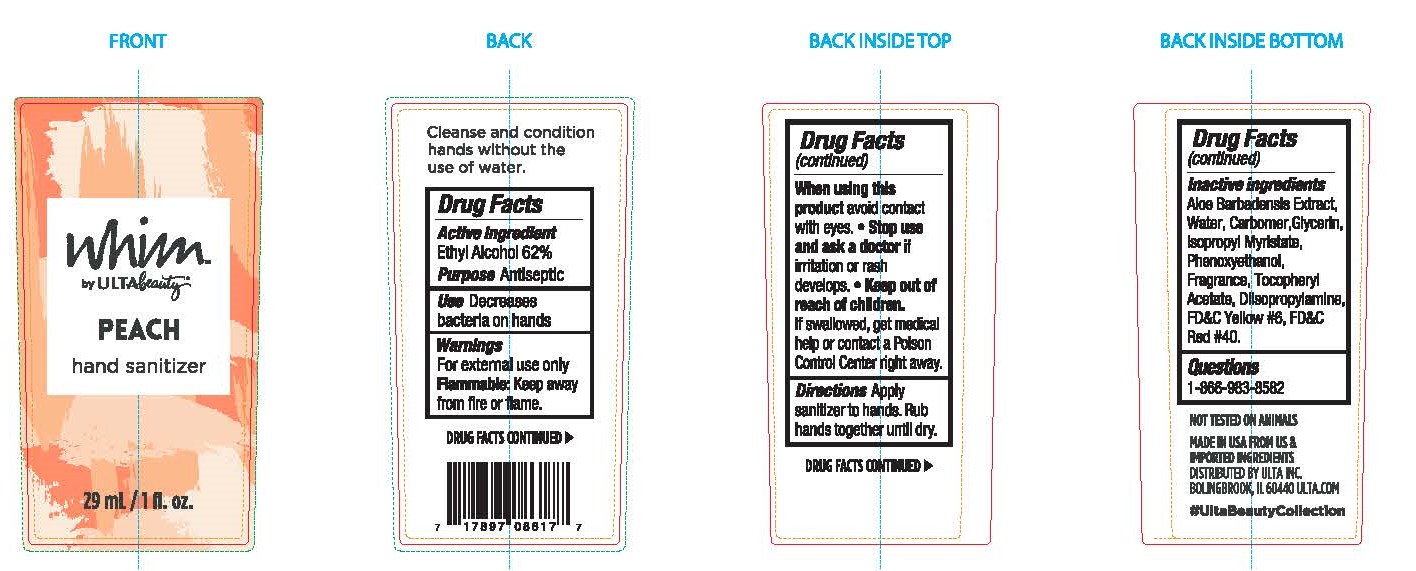 DRUG LABEL: Ulta WHIM Peach
NDC: 73708-622 | Form: GEL
Manufacturer: CarrollClean LLC
Category: otc | Type: HUMAN OTC DRUG LABEL
Date: 20200825

ACTIVE INGREDIENTS: ALCOHOL 62 mL/100 mL
INACTIVE INGREDIENTS: CARBOMER INTERPOLYMER TYPE A (55000 CPS) 0.4 mL/100 mL; WATER 31.5 mL/100 mL; ALOE VERA LEAF 0.9 mL/100 mL; ISOPROPYL MYRISTATE 0.09 mL/100 mL; PHENOXYETHANOL 0.05 mL/100 mL; .ALPHA.-TOCOPHEROL ACETATE 0.01 mL/100 mL; GLYCERIN 0.19 mL/100 mL; DIISOPROPYLAMINE 0.21 mL/100 mL

Ulta WHIM Peach

Directions

Cleanse and condition hands without the use of water.

Active

Ethyl Alcohol 62%

Purpose

Antiseptic

Use

Decreases bacteria on hands

Warnings

For external use only

FLAMMABLE Keep away from fire or flame.

Inactive

Aloe Barbadensis Extract, Water, Carbomer, Glycerin, Isoproypl Myristate, Phenoxyethanol, Fragrance, Tocophenyl Acetate, Diisopropylamine, FD&C Yellow #6, FD&C Red #40.

Keep out of reach of children.